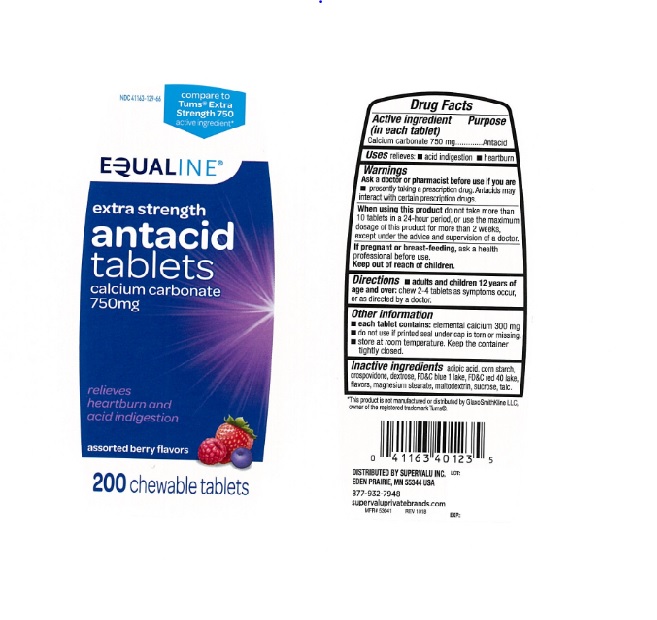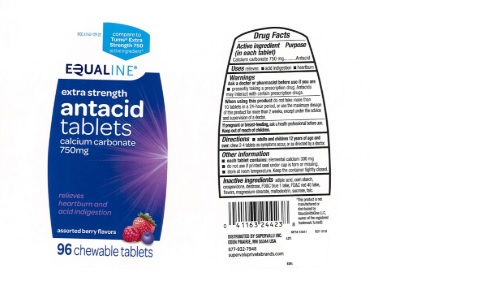 DRUG LABEL: Equaline Extra Strength Assorted Berry Antacid
NDC: 41163-129 | Form: TABLET, CHEWABLE
Manufacturer: UNITED NATURAL FOODS, INC. DBA UNFI
Category: otc | Type: Human OTC Drug Label
Date: 20240501

ACTIVE INGREDIENTS: CALCIUM CARBONATE 750 mg/1 1
INACTIVE INGREDIENTS: STARCH, CORN; DEXTROSE, UNSPECIFIED FORM; MAGNESIUM STEARATE; MALTODEXTRIN; SUCROSE; TALC; CROSPOVIDONE; ADIPIC ACID; FD&C BLUE NO. 1; FD&C RED NO. 40

Equaline Extra Strength Assorted Berry Antacid 127

ACTIVE INGREDIENT (in each tablet)

Calcium carbonate 750 mg

PURPOSE

Antacid

USE(S)

relieves:

- acid indigestion
- heartburn

WARNINGS

.

ASK A DOCTOR OR PHARMACIST BEFORE USE IF YOU ARE

- presently taking a prescription drug. Antacids may interact with certain prescription drugs.

WHEN USING THIS PRODUCT

do not take more than 10 tablets in a 24-hour period, or use the maximum dosage of this product for more than 2 weeks, except under the advice and supervision of a doctor.

IF PREGNANT OR/BREASTFEEDING,

ask a health professional before use.

KEEP OUT OF REACH OF CHILDREN

.

DIRECTIONS

- adults and children 12 years of age and over: chew 2-4 tablets as symptoms occur, or as directed by a doctor.

OTHER INFORMATION

- each tablet contains: elemental calcium 300 mg,
- do not use if printed seal under cap is torn or missing.
- store at room temperature. Keep the container tightly closed..

INACTIVE INGREDIENTS

adipic acid, corn starch, crospovidone, dextrose, FD&C blue 1 lake, FD&C red 40 lake, flavors, magnesium stearate, maltodextrin, sucrose, talc.

PRINCIPAL DISPLAY PANEL

NDC 41163-129-66

EQUALINE

compare to TUMS® Extra Strength 750 active ingredient*

extra strength
antacid tablets

calcium carbonate 750mg

relieves

heartburn and

acid indigestion

assorted berry flavors
200 CHEWABLE TABLETS

NDC 41163-129-22

EQUALINE

compare to TUMS® Extra Strength 750 active ingredient*

extra strength
antacid tablets

calcium carbonate 750mg

relieves

heartburn and

acid indigestion

assorted berry flavors
96 CHEWABLE TABLETS